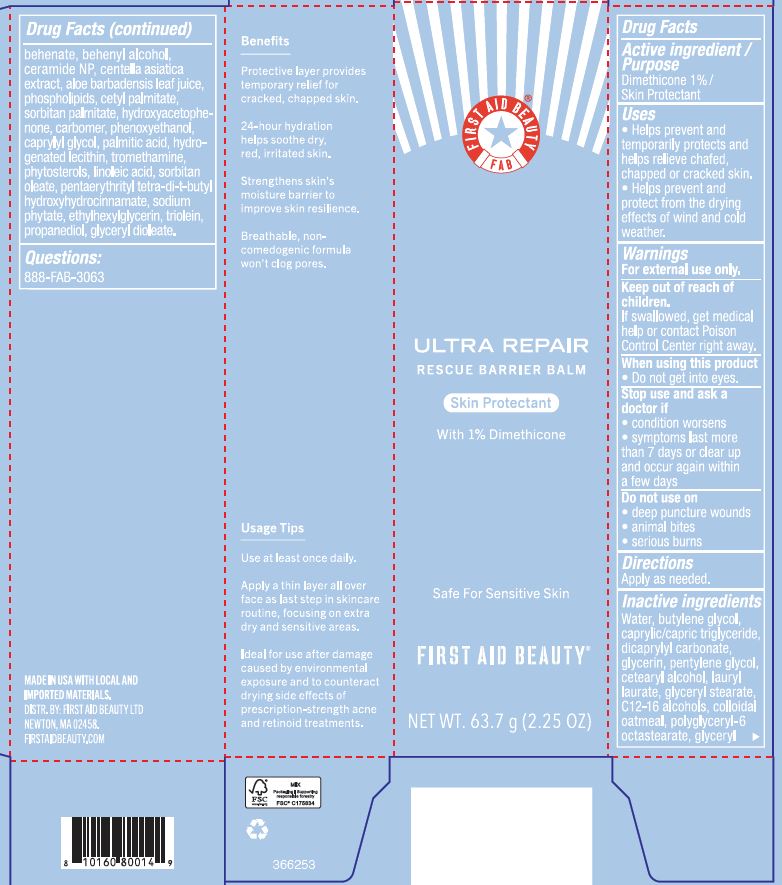 DRUG LABEL: First Aid Beauty FAB Ultra Repair Rescue Barrier Balm Skin Protectant
NDC: 84126-045 | Form: CREAM
Manufacturer: The Procter & Gamble Manufacturing Company
Category: otc | Type: HUMAN OTC DRUG LABEL
Date: 20251218

ACTIVE INGREDIENTS: DIMETHICONE 1 g/100 g
INACTIVE INGREDIENTS: PENTAERYTHRITYL TETRA-DI-T-BUTYL HYDROXYHYDROCINNAMATE; DICAPRYLYL CARBONATE; LAURYL LAURATE; BEHENYL ALCOHOL; SORBITAN PALMITATE; CARBOMER HOMOPOLYMER, UNSPECIFIED TYPE; HYDROGENATED SOYBEAN LECITHIN; LINOLEIC ACID; GLYCERYL DIOLEATE; PROPANEDIOL; CETYL PALMITATE; SORBITAN OLEATE; SODIUM PHYTATE; CENTELLA ASIATICA TRITERPENOIDS; ALOE BARBADENSIS LEAF JUICE; C12-16 ALCOHOLS; HYDROXYACETOPHENONE; TROMETHAMINE; PENTYLENE GLYCOL; ETHYLHEXYLGLYCERIN; OATMEAL; PALMITIC ACID; CETEARYL ALCOHOL; TRIOLEIN; CAPRYLYL GLYCOL; PHENOXYETHANOL; WATER; GLYCERIN; GLYCERYL STEARATE; CAPRYLIC/CAPRIC TRIGLYCERIDE; CERAMIDE NP; BUTYLENE GLYCOL

First Aid Beauty FAB Ultra Repair Rescue Barrier Balm Skin Protectant

Drug Facts

Active ingredients

Dimethicone 1%

Purpose

Skin Protectant

Uses

- Helps prevent and temporarily protects and helps relieve chafed, chapped or cracked skin.
- Helps prevet and protect from the drying effects of wind and cold weather.

WARNINGS

For external use only

Keep out of reach of children. If swallowed, get medical help or contact a Poison Control Center right away.

WHEN USING

Do not get into eyes.

Stop use and ask a doctor if condition worsens, symptoms last more than 7 days or clear up and occur again within a few days

Do not use on

- deep puncture wounds
- animal bites
- serious burns

Directions

Apply as needed

INACTIVE INGREDIENT

WATER, BUTYLENE GLYCOL, CAPRYLIC/CAPRIC TRIGLYCERIDE, DICAPRYLYL CARBONATE, GLYCERIN, PENTYLENE GLYCOL, CETEARYL ALCOHOL, LAURYL LAURATE, GLYCERYL STEARATE, C12-16 ALCOHOLS, COLLOIDAL OATMEAL, POLYGLYCERYL-6 OCTASTEARATE, GLYCERYL BEHENATE, BEHENYL ALCOHOL, CERAMIDE NP, CENTELLA ASIATICA EXTRACT, ALOE BARBADENSIS LEAF JUICE, PHOSPHOLIPIDS, CETYL PALMITATE, SORBITAN PALMITATE, HYDROXYACETOPHENONE, CARBOMER, PHENOXYETHANOL, CAPRYLYL GLYCOL, PALMITIC ACID, HYDROGENATED LECITHIN, TROMETHAMINE, PHYTOSTEROLS, LINOLEIC ACID, SORBITAN OLEATE, PENTAERYTHRITYL TETRA-DI-T-BUTYL HYDROXYHYDROCINNAMATE, SODIUM PHYTATE, ETHYLHEXYLGLYCERIN, TRIOLEIN, PROPANEDIOL, GLYCERYL DIOLEATE

Questions:

888-FAB-3063

MADE IN USA

FIRST AID BEAUTY LTD

NEWTON, MA 02458

WWW.FIRSTAIDBEAUTY.COM

PRINCIPAL DISPLAY PANEL - 63.7 g (2.25 oz)

First Aid Beauty

FAB

Ultra Repair®

Rescue Barrier Balm

Skin Protectant

with 1% Dimethicone

Net Wt. 63.7 g (2.25 oz)